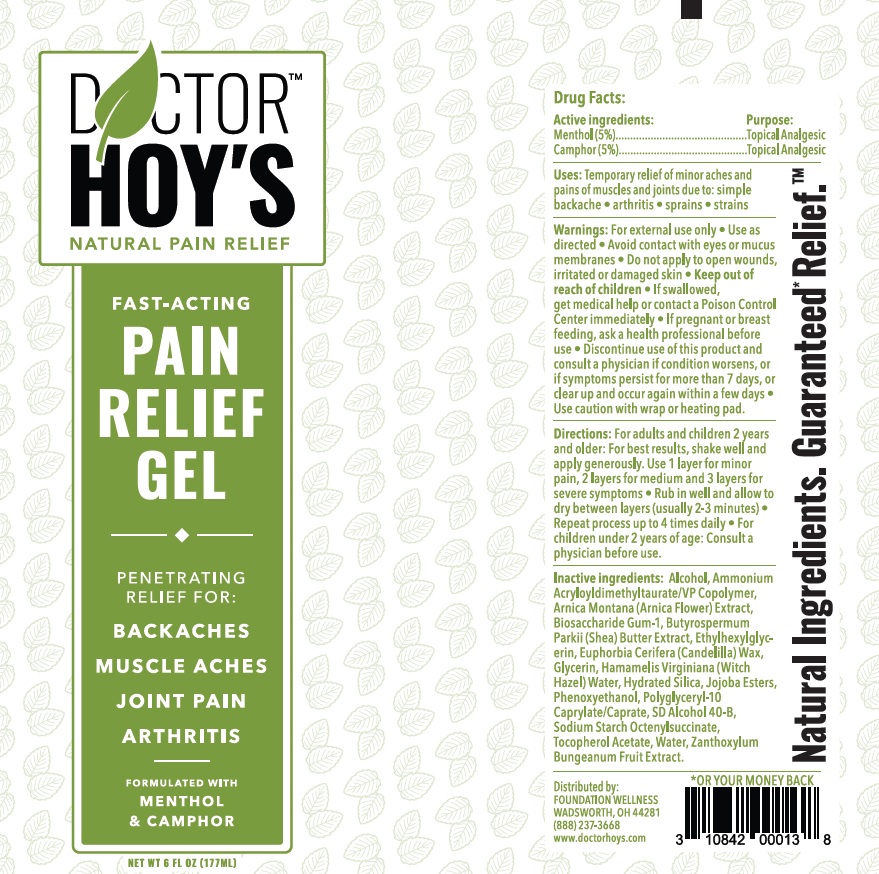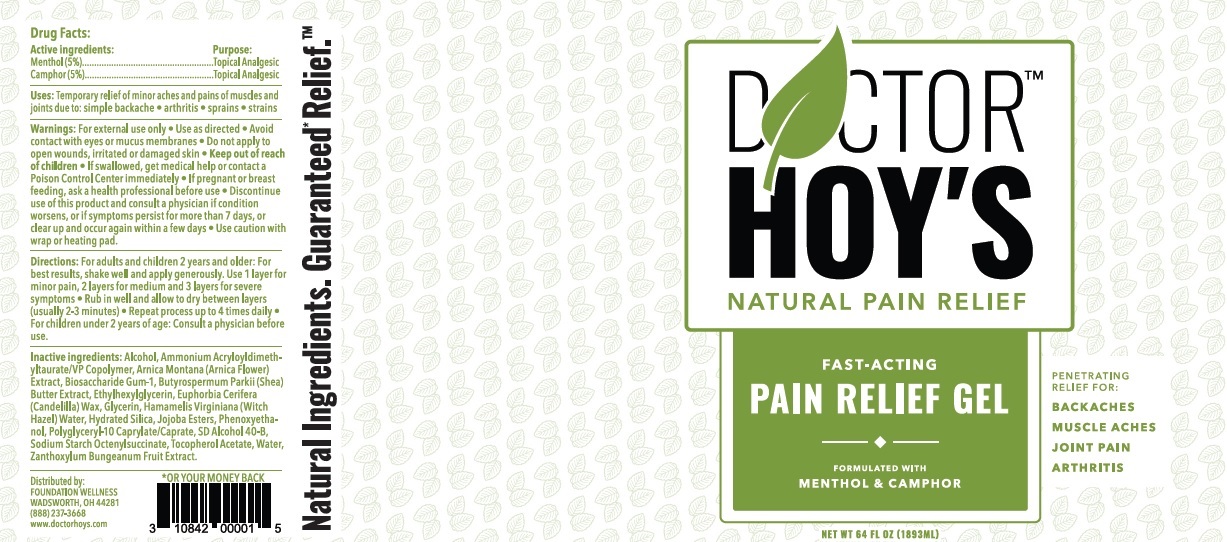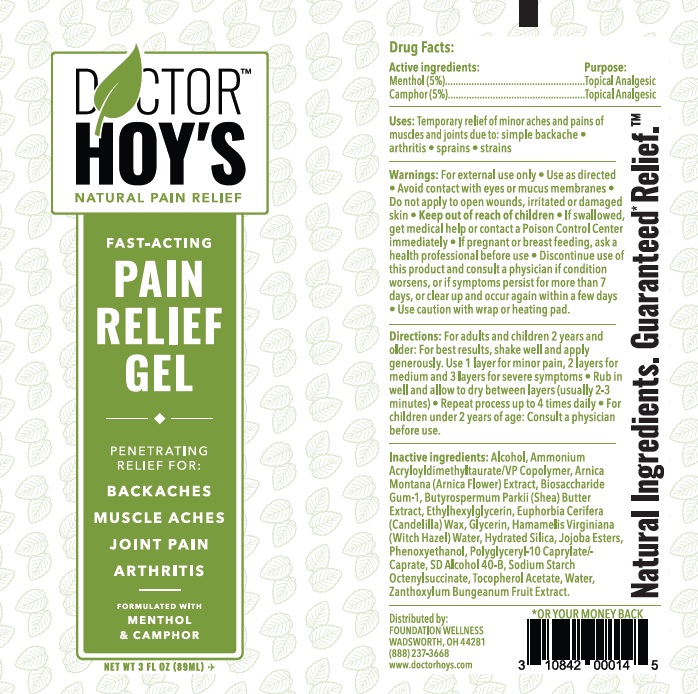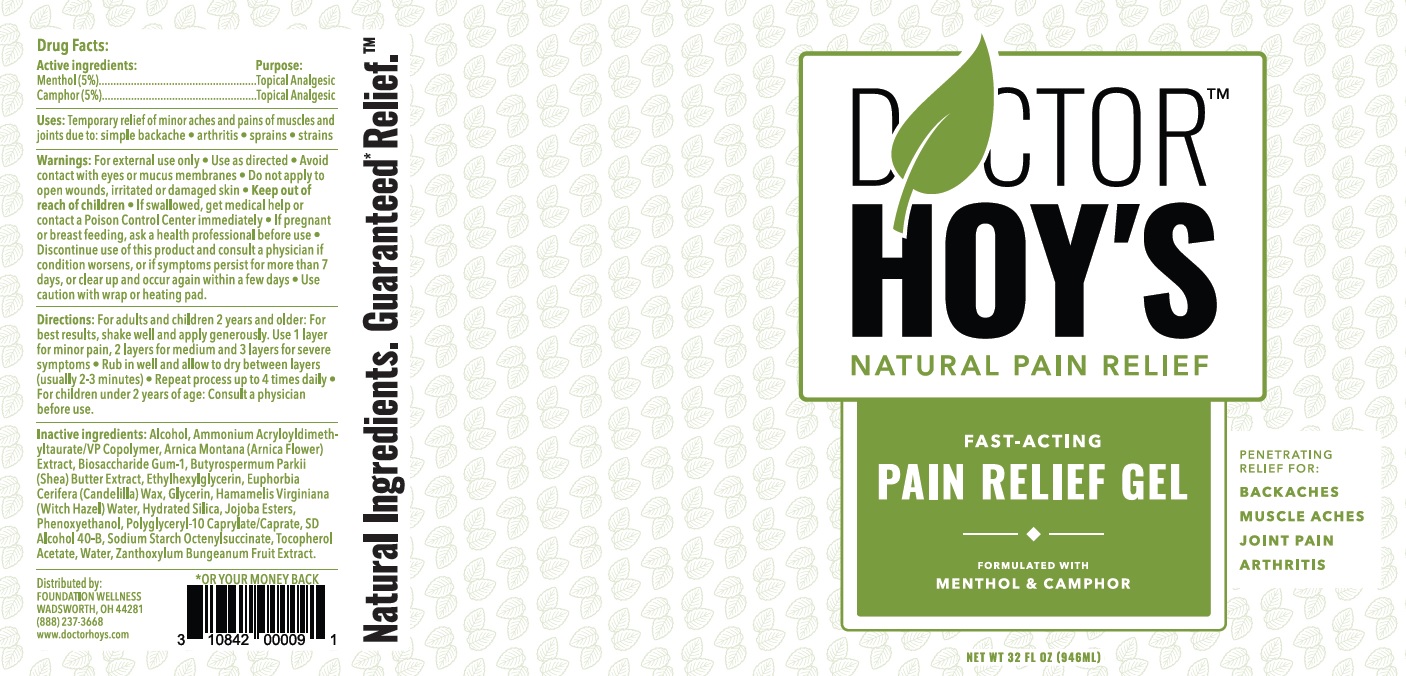 DRUG LABEL: Doctor Hoys Pain Relief Gel
NDC: 75638-010 | Form: GEL
Manufacturer: Dynamic Blending Specialists, Inc.
Category: otc | Type: HUMAN OTC DRUG LABEL
Date: 20260102

ACTIVE INGREDIENTS: MENTHOL 50 mg/1 mL; CAMPHOR (SYNTHETIC) 50 mg/1 mL
INACTIVE INGREDIENTS: ALCOHOL; ARNICA MONTANA WHOLE; BIOSACCHARIDE GUM-1; SHEA BUTTER; ETHYLHEXYLGLYCERIN; CANDELILLA WAX; GLYCERIN; HAMAMELIS VIRGINIANA TOP WATER; HYDRATED SILICA; PHENOXYETHANOL; .ALPHA.-TOCOPHEROL ACETATE; WATER; ZANTHOXYLUM BUNGEANUM FRUIT; AMMONIUM ACRYLOYLDIMETHYLTAURATE/VP COPOLYMER

Doctor Hoy's Pain Relief Gel

Active ingredients:

Menthol (5%)

Camphor (5%)

Purpose:

Topical Analgesic

Uses:

Temporary relief of minor aches and pains of muscles and joints due to: simple backache • arthritis • sprains • strains

Warnings:

• For external use only

• Use as directed

• Avoid contact with eyes or mucus membranes

• Do not apply to open wounds, irritated or damaged skin

Keep Out of reach of children

If swallowed, get medical help or contact a Poison Control Center immediately

If pregnant or breast feeding,

• ask a health professional before use

• Discontinue use of this product and consult a physician if condition worsens, or if symptoms persist for more than 7 days, or clear up and occur again within a few days

• Use caution with wrap or heating pad.

Directions:

For adults and children 2 years and older: For best results, shake well and apply generously. Use 1 layer for minor pain, 2 layers for medium and 3 layers for severe symptoms • Rub in well and allow to dry between layers (usually 2-3 minutes) • Repeat process up to 4 times daily • for children under 2 years of age: Consult a physician before use.

Inactive ingedients:

Alcohol, Ammonium Acryloyldimethyltaurate/VP Copolymer, Arnica Montana (Arnica Flower) Extract, Biosaccharide Gum-1, Butyrospermum Parkii (Shea) Butter Extract, Ethylhexylglycerin, Euphorbia Cerifera (Candelilla) Wax, Glycerin, Hamamelis Virginiana (Witch Hazel) Water, Hydrated Silica, Jojoba Esters, Phenoxyethanol, Polyglyceryl-10 Caprylate/Caprate, SD Alcohol 40-B, Sodium Starch Octenylsuccinate, Tocopherol Acetate, Water, Zanthoxylum Bungeanum Fruit Extract.